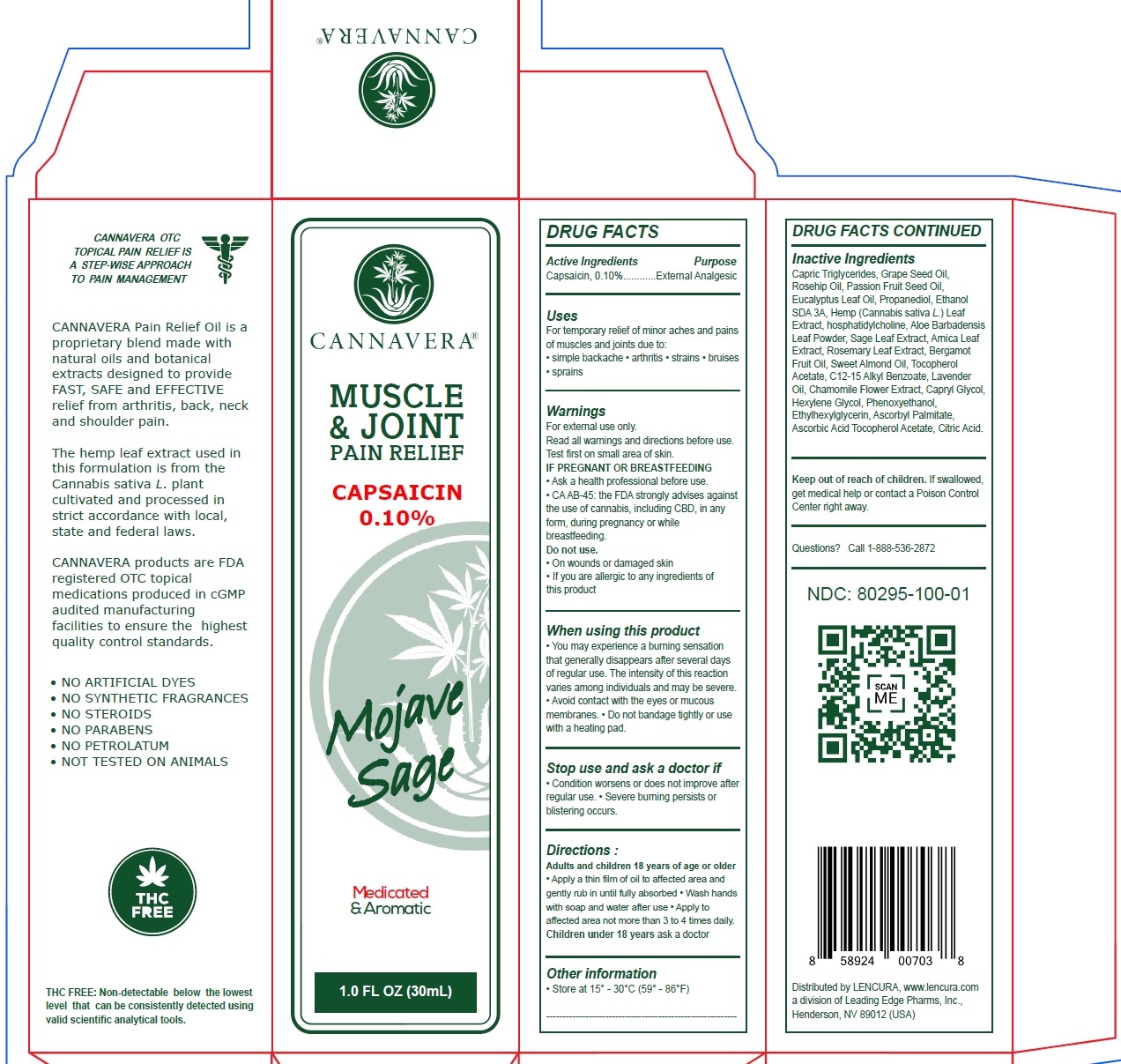 DRUG LABEL: CANNAVERA PAIN RELIEF
NDC: 80295-100 | Form: OIL
Manufacturer: Leading Edge Pharms, Inc.
Category: otc | Type: HUMAN OTC DRUG LABEL
Date: 20230817

ACTIVE INGREDIENTS: CAPSAICIN 1 mg/1 mL
INACTIVE INGREDIENTS: TRICAPRIN; GRAPE SEED OIL; EUCALYPTUS OIL; PROPANEDIOL; CANNABIS SATIVA WHOLE; ALOE VERA LEAF; SAGE; ROSEMARY; ALMOND OIL; .ALPHA.-TOCOPHEROL ACETATE; ALKYL (C12-15) BENZOATE; LAVENDER OIL; CAPRYLYL GLYCOL; HEXYLENE GLYCOL; PHENOXYETHANOL; ETHYLHEXYLGLYCERIN; ASCORBYL PALMITATE; ASCORBIC ACID; CITRIC ACID MONOHYDRATE

CANNAVERA PAIN RELIEF OIL

Active Ingredients

Capsaicin, 0.10%

Purpose

External Analgesic

Uses

For temporary relief of minor aches and pains of muscles and joints due to:
• simple backache • arthritis • strains • bruises • sprains

Warnings

For external use only.
Read all warnings and directions before use.
Test first on small area of skin.

IF PREGNANT OR BREASTFEEDING

• Ask a health professional before use.
• CA AB-45: the FDA strongly advises against the use of cannabis, including CBD, in any form, during pregnancy or while breastfeeding.

Do not use.

• If you are allergic to any ingredients of this product

When using this product

• You may experience a burning sensation that generally disappears after several days of regular use. The intensity of this reaction varies among individuals and may be severe.
• Avoid contact with the eyes or mucous membranes. • Do not bandage tightly or use with a heating pad.

Stop use and ask a doctor if

• Condition worsens or does not improve after regular use. • Severe burning persists or blistering occurs.

Keep out of reach of children.

If swallowed, get medical help or contact a Poison Control Center right away.

Directions:

Adults and children 18 years of age or older
• Apply a thin film of oil to affected area and gently rub in until fully absorbed • Wash hands with soap and water after use • Apply to affected area not more than 3 to 4 times daily.
Children under 18 yearsask a doctor

Other information

• Store at 15° - 30°C (59° - 86°F)

Inactive Ingredients

Capric Triglycerides, Grape Seed Oil, Rosehip Oil, Passion Fruit Seed Oil, Eucalyptus Leaf Oil, Propanediol, Ethanol SDA 3A, Hemp (Cannabis sativa L.) Leaf Extract, hosphatidylcholine, Aloe Barbadensis Leaf Powder, Sage Leaf Extract, Arnica Leaf Extract, Rosemary Leaf Extract, Bergamot Fruit Oil, Sweet Almond Oil, Tocopherol Acetate, C12-15 Alkyl Benzoate, Lavender Oil, Chamomile Flower Extract, Capryl Glycol, Hexylene Glycol, Phenoxyethanol, Ethylhexylglycerin, Ascorbyl Palmitate, Ascorbic Acid Tocopherol Acetate, Citric Acid.

Questions?

Call 1-888-536-2872